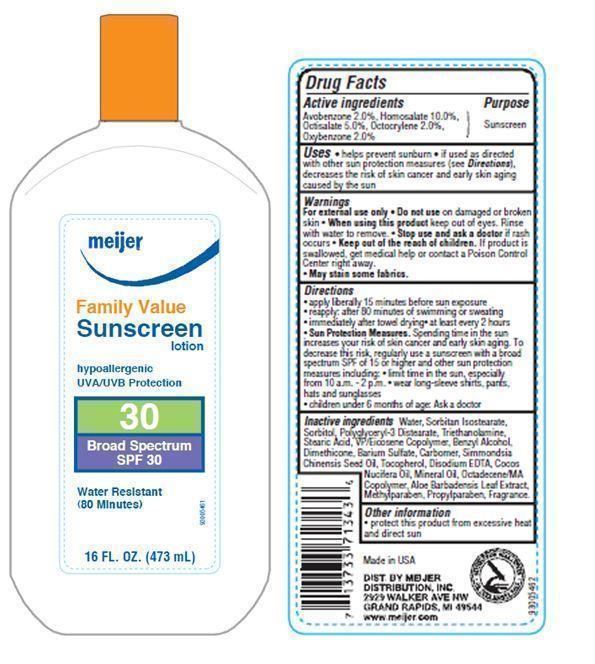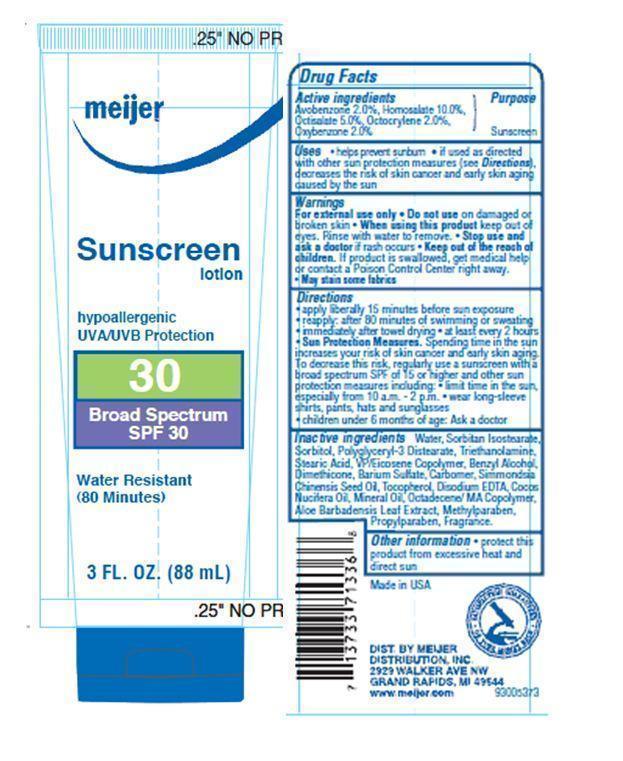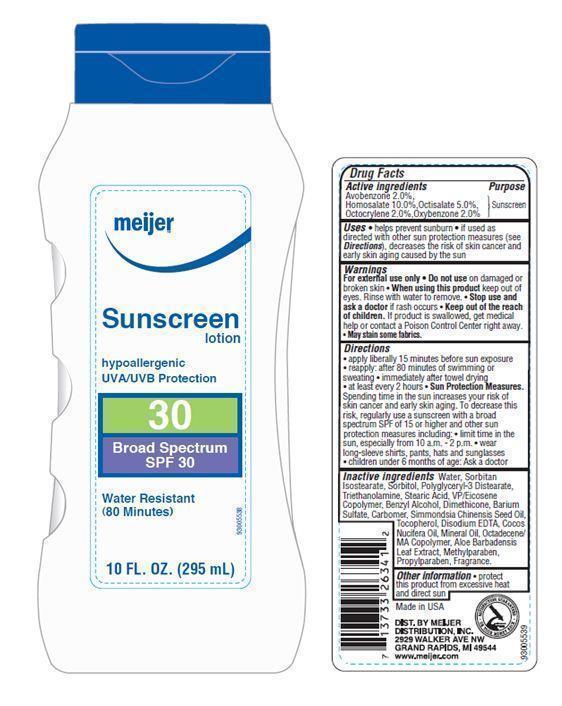 DRUG LABEL: Meijer SPF 30
NDC: 41250-005 | Form: LOTION
Manufacturer: Meijer Distribution Inc
Category: otc | Type: HUMAN OTC DRUG LABEL
Date: 20120101

ACTIVE INGREDIENTS: AVOBENZONE 2 mL/100 mL; HOMOSALATE 10 mL/100 mL; OCTISALATE 5 mL/100 mL; OCTOCRYLENE 2 mL/100 mL; OXYBENZONE 2 mL/100 mL
INACTIVE INGREDIENTS: WATER; SORBITAN ISOSTEARATE; SORBITOL; POLYGLYCERYL-3 DIISOSTEARATE; TROLAMINE; STEARIC ACID; BENZYL ALCOHOL; DIMETHICONE; BARIUM SULFATE; CARBOMER HOMOPOLYMER TYPE C (ALLYL PENTAERYTHRITOL CROSSLINKED); JOJOBA OIL; TOCOPHEROL; EDETATE DISODIUM; COCONUT OIL; MINERAL OIL; ALOE VERA LEAF; METHYLPARABEN; PROPYLPARABEN

Drug Facts

Active Ingredients

Avobenzone 2.0%
Homosalate 10.0%
Octisalate 5.0%
Octocrylene 2.0%
Oxybenzone 2.0%

Purpose

Sunscreen

Uses

- Helps prevent sunburn
- If used as directed with other sun protection measures (see Directions), decrease the risk of skin cancer and early skin aging caused by the sun.

Warnings

For external use only. Do not use on damaged or broken skin. May stain some fabrics.

When using this product

Keep out of eyes. Rinse with water to remove.

stop use and ask a doctor

if rash occurs

Keep out of reach of children

If swallowed, get medical help or contact a Poison Control Center right away.

Directions

- apply liberally 15 minutes before sun exposure
- reapply
- after 80 minutes of swimming or sweating
- immediately after towel drying
- at least every 2 hours
- Sun Protection Measures: Spending time in the sun increases your risk of skin cancer and early skin aging. To decrease this risk, regularly use a sunscreen with a broad spectrum SPF of 15 or higher and other sun protection measures including:
- limit time in the sun, especially from 10 a.m. - 2 p.m.
- wear long-sleeve shirts, pants, hats and sunglasses
- children under 6 months of age: Ask a doctor

Inactive Ingredients

Water, Sorbitan Isostearate, Sorbitol, Polyglyceryl-3 Distearate, Triethanolamine, Stearic Acid, VP/Eicosene Copolymer, Benzyl Alcohol, Dimethicone, Barium Sulfate, Carbomer, Simmondsia Chinensis (Jojoba) Seed Oil, Tocopherol, Disodium EDTA, Cocos Nucifera (Coconut) Oil, Mineral Oil, Octadecene/MA Copolymer, Aloe Barbadensis Leaf Extract, Methylparaben, Propylparaben, Fragrance.

Other Information

Protect this product from excessive heat and direct sun.